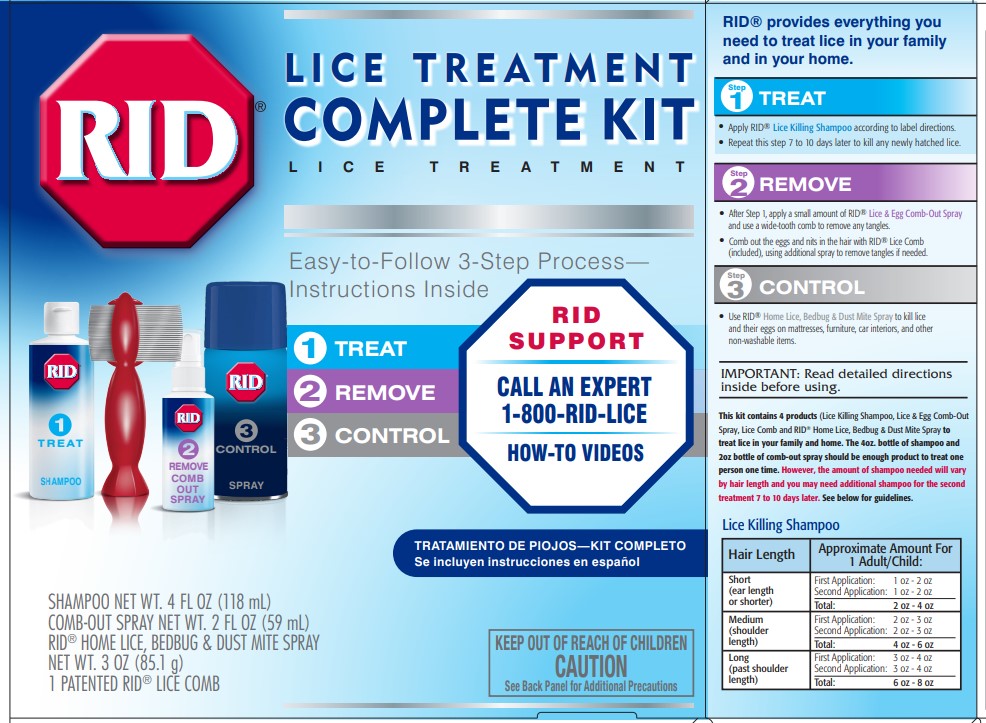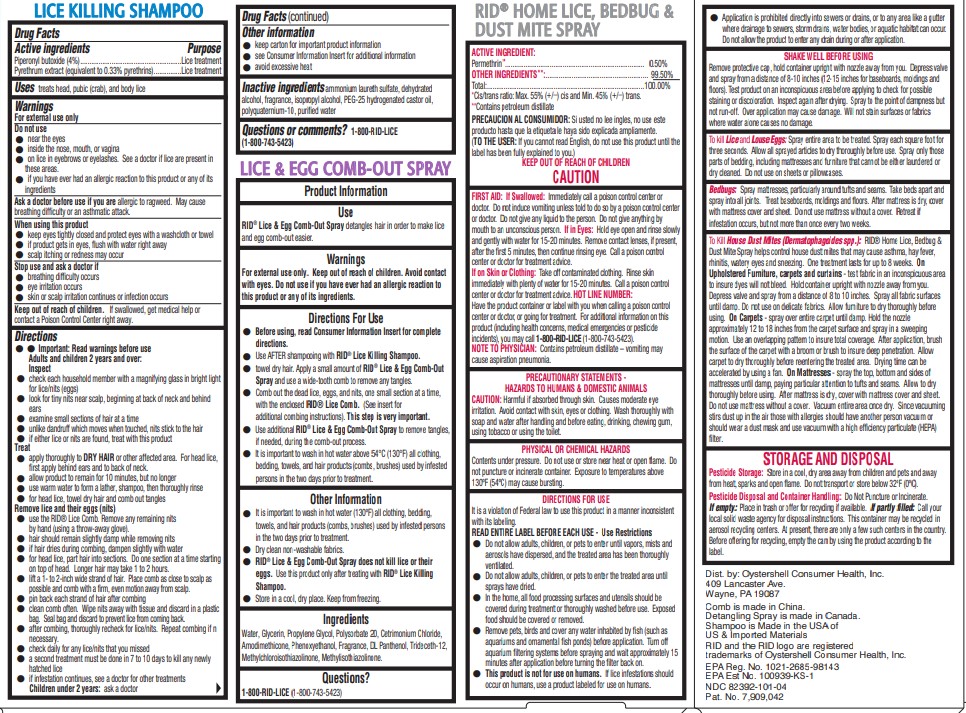 DRUG LABEL: RID Lice Treatment Complete Kit
NDC: 82392-101 | Form: KIT | Route: TOPICAL
Manufacturer: Oystershell Consumer Health Inc
Category: otc | Type: HUMAN OTC DRUG LABEL
Date: 20250702

ACTIVE INGREDIENTS: PIPERONYL BUTOXIDE 40 mg/1 mL; PYRETHRUM EXTRACT 0.033 mg/1 mL
INACTIVE INGREDIENTS: AMMONIUM LAURETH-2 SULFATE; ALCOHOL; ISOPROPYL ALCOHOL; PEG-25 HYDROGENATED CASTOR OIL; POLYQUATERNIUM-10 (125 MPA.S AT 2%); WATER

RID®Lice Treatment Complete Kit
Drug Facts

Active ingredients

Piperonyl butoxide (4%)

Pyrethrum extract (equivalent to 0.33% pyrethrins)

Purpose

Lice treatment

Uses

treats head, pubic (crab), and body lice

Warnings

For external use only

Do not use

- near the eyes
- inside nose, mouth, or vagina
- on lice in eyebrows or eyelashes. See a doctor if lice are present in these areas.
- If you have ever had an allergic reaction to this product or any of its ingredients

Ask a doctor before use if you are

allergic to ragweed. May cause breathing difficulty or an asthmatic attack.

When using this product

- keep eyes tightly closed and protect eyes with a washcloth or towel
- if product gets into eyes, flush with water right away
- scalp itching or redness may occur

Stop use and ask a doctor if

- breathing difficulty occurs
- eye irritation occurs
- skin or scalp irritation continues or infection occurs

Keep out of reach of children.

If swallowed, get medical help or contact a Poison Control Center right away.

Directions

● ● Important: Read warnings before use
Adults and children 2 years and over:
Inspect

- check each household member with a magnifying glass in bright light for lice/nits (eggs)
- look for tiny nits near scalp, beginning at back of neck and behind ears
- examine small sections of hair at a time
- unlike dandruff which moves when touched, nits stick to the hair
- if either lice or nits are found, treat with this product

Treat

- apply thoroughly to DRY HAIRor other affected area. For head lice, first apply behind ears and to back of neck.
- allow product to remain for 10 minutes, but no longer
- use warm water to form a lather, shampoo, then thoroughly rinse
- for head lice, towel dry hair and comb out tangles

Remove lice and their eggs (nits)

- use the RID® Lice Comb. Remove any remaining nits by hand (using a throw-away glove).
- hair should remain slightly damp while removing nits
- if hair dries during combing, dampen slightly with water
- for head lice, part hair into sections. Do one section at a time starting on top of head. Longer hair may take 1 to 2 hours.
- lift a 1- to 2-inch wide strand of hair. Place comb as close to scalp as possible and comb with a firm, even motion away from scalp.
- pin back each strand of hair after combing
- clean comb often. Wipe nits away with tissue and discard in a plastic bag. Seal bag and discard to prevent lice from coming back.
- after combing, thoroughly recheck for lice/nits. Repeat combing if necessary.
- check daily for any lice/nits that you missed
- a second treatment must be done in 7 to 10 days to kill any newly hatched lice
- if infestation continues, see a doctor for other treatments

Children under 2 years:ask a doctor

Other information

- keep carton for important product information
- see Consumer Information Insert for additional information
- avoid excessive heat

Inactive ingredients

ammonium laureth sulfate, dehydrated alcohol, fragrance, isopropyl alcohol, PEG-25 hydrogenated castor oil, polyquaternium-10, purified water

Questions or comments?

1-800-RID-LICE
(1-800-743-5423)

Principal Display Panel

RID®

LICE TREATMENT
COMPLETE KIT
LICE TREATMENT

Easy-to-Follow 3-Step Process—
Instructions Inside

① TREAT
② REMOVE
③ CONTROL

RID
SUPPORT

CALL AN EXPERT
1-800-RID-LICE

HOW-TO VIDEOS

TRATAMIENTO DE PIOJOS—KIT COMPLETO
Se incluyen instrucciones en español

KEEP OUT OF REACH OF CHILDREN
CAUTION
See Back Panel for Additional Precautions

SHAMPOO NET WT. 4 FL OZ (118 mL)
COMB-OUT SPRAY NET WT. 2 FL OZ (59 mL)
RID®HOME LICE, BEDBUG & DUST MITE SPRAY
NET WT. 3 OZ (85.1 g)
1 PATENTED RID®LICE COMB

RID® provides everything you
need to treat lice in your family
and in your home.

Step 1 TREAT

- Apply RID®Lice Killing Shampoo according to label directions.
- Repeat this step 7 to 10 days later to kill any newly hatched lice.

Step 2 REMOVE

- After Step 1, apply a small amount of RID®Lice & Egg Comb-Out Spray and use a wide-tooth comb to remove any tangles.
- Comb out the eggs and nits in the hair with RID®Lice comb (included), using additional spray to remove tangles if needed.

Step 3 CONTROL

- Use RID®Home Lice, Bedbug & Dust Mite Spray to kill lice and their eggs on mattresses, furniture, car interiors, and other non-washable items.

IMPORTANT: Read detailed directions
inside before using.

This kit contains 4 products(Lice Killing Shampoo, Lice & Egg Comb-Out
Spray, Lice Comb and RID®Home Lice, Bedbug & Dust Mite Spray to
treat lice in your family and home. The 4oz. bottle of shampoo and
2oz bottle of comb-out spray should be enough product to treat one
person one time. However, the amount of shampoo needed will vary
by hair length and you may need additional shampoo for the second
treatment 7 to 10 days later. See below for guidelines.

Lice Killing Shampoo

Hair Length | Approximate Amount For 1 Adult/Child:
Short (ear length or shorter) | First Application: 1 oz - 2 oz Second Application: 1 oz - 2 oz Total: 2 oz - 4 oz
Medium (shoulder length) | First Application: 2 oz - 3 oz Second Application: 2 oz - 3 oz Total: 4 oz - 6 oz
Long (past shoulder length) | First Application: 3 oz - 4 oz Second Application: 3 oz - 4 oz Total: 6 oz - 8 oz